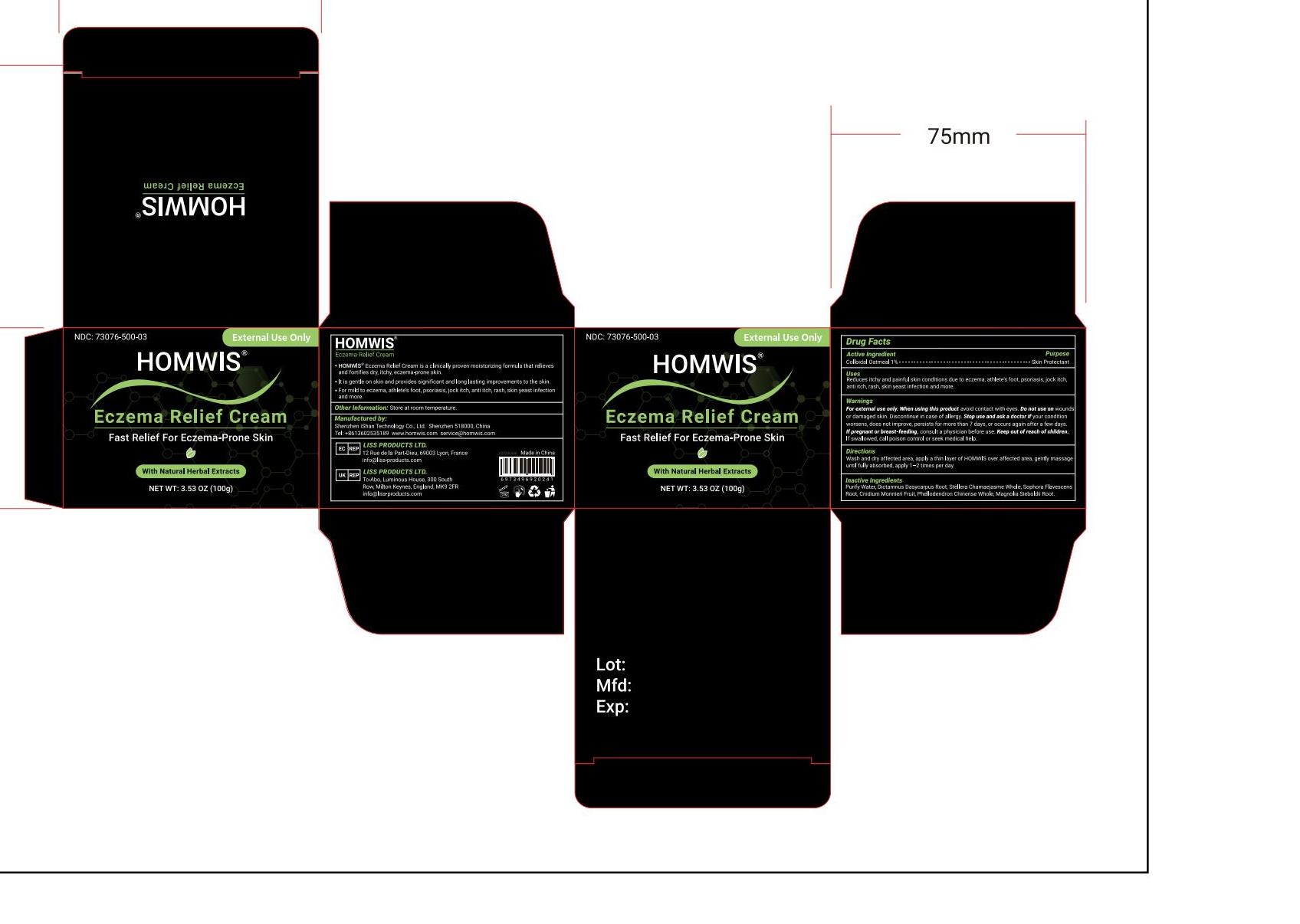 DRUG LABEL: HOMWIS Eczame Relief Cream
NDC: 73076-500 | Form: CREAM
Manufacturer: Shenzhen Ishan Technology Co., Ltd
Category: homeopathic | Type: HUMAN OTC DRUG LABEL
Date: 20260212

ACTIVE INGREDIENTS: OATMEAL 1 g/100 g
INACTIVE INGREDIENTS: WATER; DICTAMNUS DASYCARPUS ROOT; STELLERA CHAMAEJASME WHOLE; SOPHORA FLAVESCENS ROOT; CNIDIUM MONNIERI FRUIT; PHELLODENDRON CHINENSE WHOLE; MAGNOLIA SIEBOLDII ROOT

Active ingredient

Colloidal Oatmea 1%-----Skin Protectant

Inactive ingredient

Purify Water, Dictamnus Dasycarpus Root, Stellera Chamaejasme Whole, Sophora Flavescens
Root, Cnidium Monnieri Fruit, Phellodendron Chinense Whole, Magnolia Sieboldii Root

Keep out of reach of children.

if swallowed, call poison control or seek medical help.

Ask a doctor if

your condition worsens, does not improve, persists for more than 7 days, or occurs again after a few days

Stop use and ask a doctor if

pain worsens or persists, or if youexperience any of these symptoms: burning, itching, rash, or other changes in theskin where the product was placed.

USES

Reduces itchy and painful skin conditions due to eczema, athlete's foot, psoriasis, jock itch,
anti itch, rash, skin yeast infection and more

Other information

Store at room temperature

Directions

Wash and dry affected area, apply a thin layer of HOWlS over affected area, gently massage
until fully absorbed, apply 1-2 times per day.

Dosage & administration

Apply 1-2 times a day

When using this product

avoid contact with eyes

RECENT MAJOR CHANGES

no